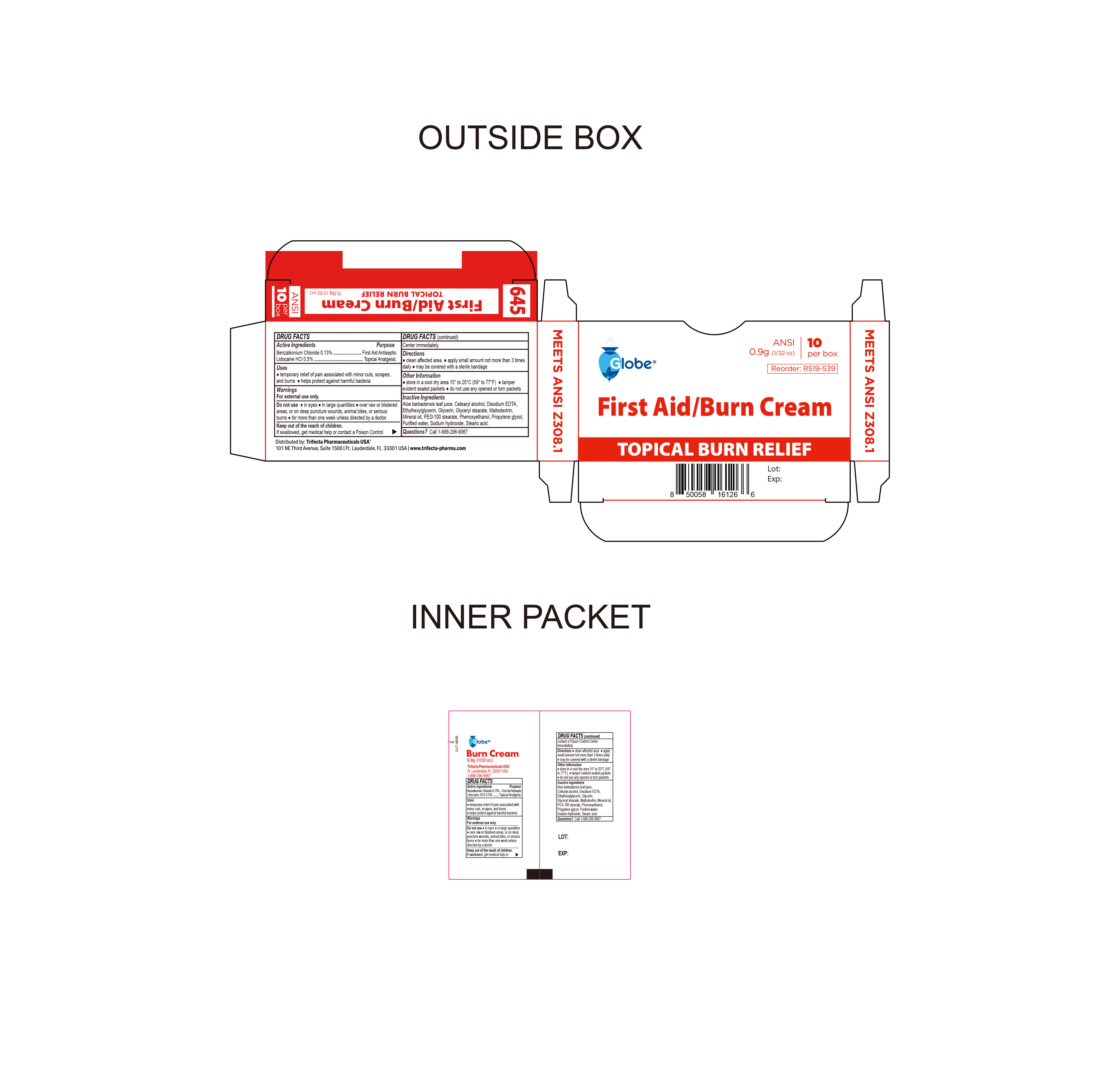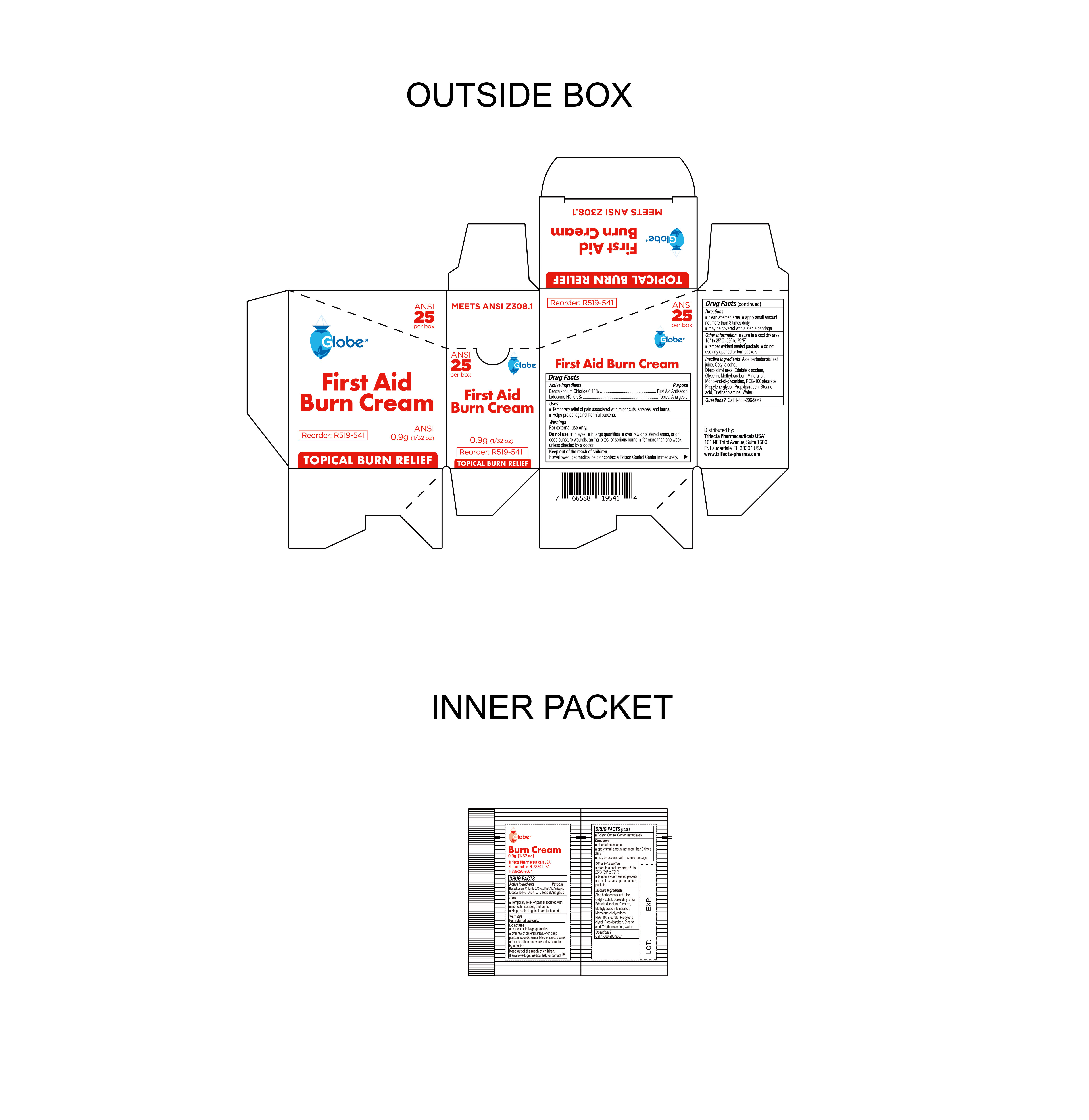 DRUG LABEL: Burn Cream
NDC: 69396-136 | Form: CREAM
Manufacturer: Trifecta Pharmaceuticals USA LLC
Category: otc | Type: HUMAN OTC DRUG LABEL
Date: 20260216

ACTIVE INGREDIENTS: LIDOCAINE HYDROCHLORIDE 0.005 g/1 g; BENZALKONIUM CHLORIDE 0.0013 g/1 g
INACTIVE INGREDIENTS: WATER; EDETATE DISODIUM; PROPYLENE GLYCOL; ALOE VERA LEAF; MINERAL OIL; STEARIC ACID; GLYCERIN; TROLAMINE; GLYCERYL MONO AND DIPALMITOSTEARATE; DIAZOLIDINYL UREA; METHYLPARABEN; CETYL ALCOHOL; PEG-100 STEARATE; PROPYLPARABEN

Globe First Aid Burn Cream

Active Ingredient

Lidocaine HCL 0.5%

Purpose

Topical Analgesic

ACTIVE INGREDIENT

Benzalkonium Chloride 0.13%

Purpose

First Aid Antiseptic

Uses

Temporary Relief of pain associated with minor cuts, scrapes and burns.

Helps protect against harmful bacteria.

Warnings

For external Use Only

Do not use

- in eyes
- in large quantities
- over raw or blistered areas, or on deep puncture wounds, animal bites, or serious burns
- for more than one week unless directed by a doctor

Directions

- Clean the affected area
- Apply a small amount not more than 3 times daily
- May be covered with a sterile bandage

Inactive Ingredients

Aloe barbadensis leaf juice, Cetyl alcohol, Diazolidinyl urea, Edetate disodium, glycerin, methylparaben, Mineral oil, Mono and di glycerides, PEG-100 stearate, propylene glycol, propylparaben, stearic acid, triethanolamine, water

Questions

Call: 1-888-296-9067

Storage Information

- Store in cool dry area 15° to 25°C (59° to 77°F).
- tamper evident sealed packets
- do not use any opened or torn packets

Keep out of reach of children

If swallowed, get medical help or contact a Poison Control Center immediately.

Other Information

Distributed By:

Trifecta Pharmaceuticals USA®

101 NE Third Ave. Ste 1500

Ft. Lauderdale, FL. 33301 USA

www.trifecta-pharma.com